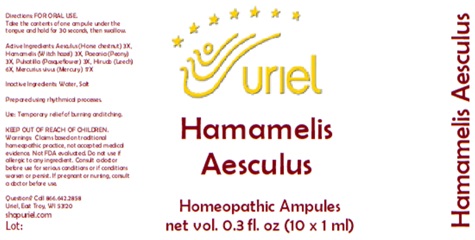 DRUG LABEL: Hamamelis Aesculus
NDC: 48951-5031 | Form: LIQUID
Manufacturer: Uriel Pharmacy Inc.
Category: homeopathic | Type: HUMAN OTC DRUG LABEL
Date: 20250125

ACTIVE INGREDIENTS: HORSE CHESTNUT 3 [hp_X]/1 mL; HAMAMELIS VIRGINIANA TOP 3 [hp_X]/1 mL; PAEONIA OFFICINALIS ROOT 3 [hp_X]/1 mL; PULSATILLA VULGARIS 3 [hp_X]/1 mL; HIRUDIN 6 [hp_X]/1 mL; MERCURY 17 [hp_X]/1 mL
INACTIVE INGREDIENTS: SODIUM CHLORIDE; WATER

Hamamelis Aesculus

INDICATIONS AND USAGE

Directions: FOR ORAL USE.

DOSAGE AND ADMINISTRATION

Take the contents of one ampule under the tongue and hold for 30 seconds, then swallow.

ACTIVE INGREDIENT

Active Ingredients: Aesculus (Horse chestnut) 3X, Hamamelis (Witch hazel) 3X, Paeonia (Peony) 3X, Pulsatilla (Pasqueflower) 3X, Hirudo (Leech) 3X, Mercurius vivus (Mercury) 17X

Inactive Ingredients: Water, Salt

Prepared using rhythmical processes.

PURPOSE

Uses: Temporary relief of burning and itching due to varicose veins or hemorrhoids.

KEEP OUT OF REACH OF CHILDREN.

WARNINGS

Warnings: Claims based on traditional homeopathic practice, not accepted medical evidence. Not FDA evaluated. Do not use if allergic to any ingredient. Consult a doctor before use for serious conditions or if conditions worsen or persist. If pregnant or nursing, consult a doctor before use.

Questions? Call 866.642.2858
Uriel, East Troy, WI 53120
shopuriel.com

Lot: